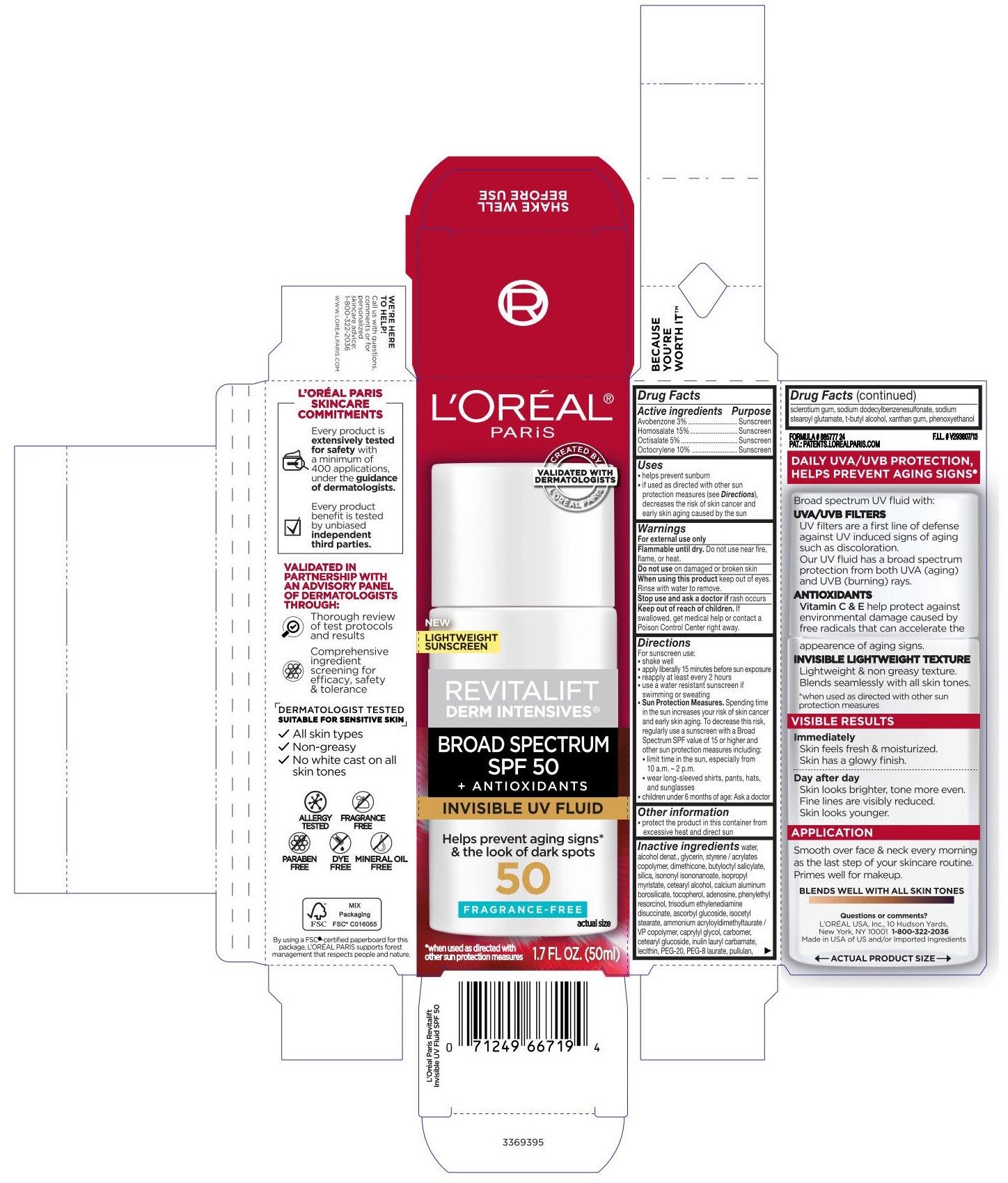 DRUG LABEL: LOreal Paris Revitalift Derm Intensives Invisible UV Fluid Broad Spectrum SPF 50 Sunscreen
NDC: 11090-099 | Form: GEL
Manufacturer: Beauty Manufacturing Solutions Corp.
Category: otc | Type: HUMAN OTC DRUG LABEL
Date: 20221206

ACTIVE INGREDIENTS: HOMOSALATE 150 mg/1 mL; OCTISALATE 150 mg/1 mL; AVOBENZONE 30 mg/1 mL; OCTOCRYLENE 100 mg/1 mL
INACTIVE INGREDIENTS: WATER; ASCORBYL GLUCOSIDE; POLYETHYLENE GLYCOL 1000; ADENOSINE; ALCOHOL; CAPRYLYL GLYCOL; CALCIUM ALUMINUM BOROSILICATE; BUTYLOCTYL SALICYLATE; BETASIZOFIRAN; PULLULAN; SODIUM STEAROYL GLUTAMATE; PHENYLETHYL RESORCINOL; TRISODIUM ETHYLENEDIAMINE DISUCCINATE; ISONONYL ISONONANOATE; PHENOXYETHANOL; SILICON DIOXIDE; GLYCERIN; ISOPROPYL MYRISTATE; TERT-BUTYL ALCOHOL; INULIN LAURYL CARBAMATE; ISOCETYL ISOSTEARATE; CETEARYL GLUCOSIDE; .ALPHA.-TOCOPHEROL, DL-; XANTHAN GUM; CETOSTEARYL ALCOHOL; DIMETHICONE

LOreal Paris Revitalift Derm Intensives Invisible UV Fluid Broad Spectrum SPF 50 Sunscreen

ACTIVE INGREDIENT

Avobenzone 3%

Homosalate 15%

Octisalate 5%

Octocrylene 10%

PURPOSE

Avobenzone 3%-Sunscreen

Homosalate 15%-Sunscreen

Octisalate 5%-Sunscreen

Octocrylene 10%-Sunscreen

USES

helps prevent sunburn
if used as directed with other sun protection measures (see Directions), decreases the risk of skin cancer and early skin aging caused by the sun

WARNINGS

For external use only

FLAMMABLE UNTIL DRY.

Do not use near fire, flame, or heat.

DO NOT USE

on damaged or broken skin

WHEN USING

keep out of eyes. Rinse with water to remove.

STOP USE

rash occurs

KEEP OUT OF REACH OF CHILDREN

If swallowed, get medical help or contact a Poison Control Center right away.

DIRECTIONS

For sunscreen use:

shake well
apply liberally 15 minutes before sun exposure
reapply at least every 2 hours
use a water resistant sunscreen if swimming or sweating
Sun Protection Measures. Spending time in the sun increases your risk of skin cancer and early skin aging. To decrease this risk, regularly use a sunscreen with a Broad Spectrum SPF value of 15 or higher and other sun protection measures including:
limit time in the sun, especially from 10 a.m. - 2 p.m.
wear long-sleeved shirts, pants, hats, and sunglasses
children under 6 months of age: Ask a doctor

OTHER INFORMATION

protect the product in this container from excessive heat and direct sun

INACTIVE INGREDIENT

water, alcohol denat.,glycerin, styrene/acrylates copolymer dimethicone, butyloctyl salicylate,silica, Isononyl Isononanoate,Isopropyl Myristate, Cetearyl Alcohol, Calcium Aluminum Borosilicate,Tocopherol,Adenosine,Phenyl Resorcinol,Trisodium Ethylenediamine Disuccinate,Ascorbyl Glucoside,isocetyl stearate,ammonium acryloyldimethyltaurate/vp copolymer,caprylyl glycol,carbomer,cetearyl glucoside, inulin lauryl carbamate,Lecithin,PEG-20,PEG-8 laurate,pullulan,sclerotium gum,sodium dodecylbenzenesulfonate, Sodium Stearoyl Glutamate,t-Butyl Alcohol,Xanthan Gum,Phenoxyethanol